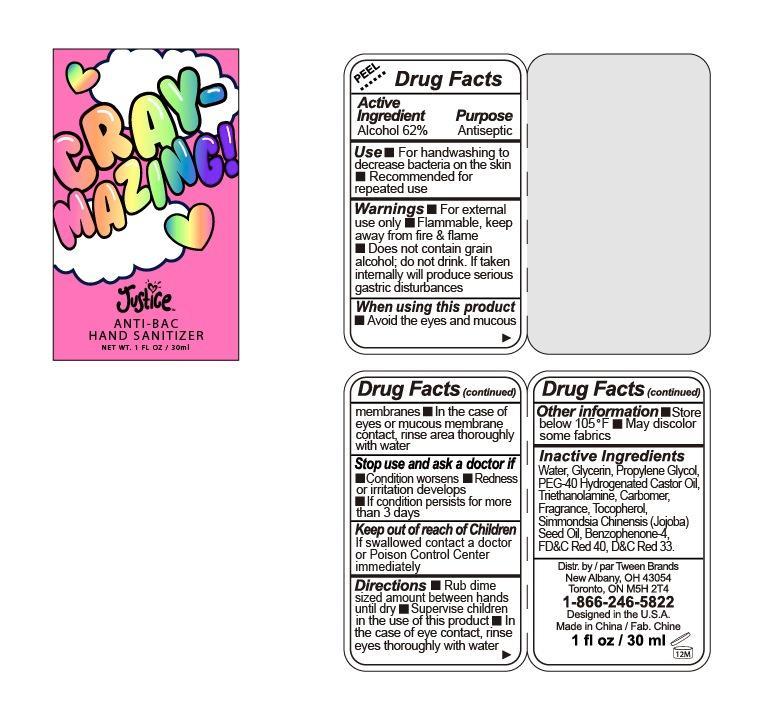 DRUG LABEL: Justice
NDC: 60637-004 | Form: LIQUID
Manufacturer: Tween Brands Inc
Category: otc | Type: HUMAN OTC DRUG LABEL
Date: 20130910

ACTIVE INGREDIENTS: ALCOHOL 62 g/100 mL
INACTIVE INGREDIENTS: WATER; GLYCERIN; PROPYLENE GLYCOL; POLYOXYL 40 HYDROGENATED CASTOR OIL; TROLAMINE; TOCOPHEROL; JOJOBA OIL; FD&C RED NO. 40; D&C RED NO. 33

Drug Facts

Active Ingredient

Alcohol 62%

Purpose

Antiseptic

Use

■ For handwashing to decrease bacteria on the skin

■ Recommended for repeated use

Warnings

■ For external use only

■ Flammable, keep away from fire and flame

■ Does not contain grain alcohol; do not drink, if taken internally will produce serious gastric disturbances

When using this product

■ Avoid the eyes and mucous membranes ■ In the case of eyes or mucous membrane contact; rinse area thoroughly with water

Stop use and ask a doctor if

■ Condition worsens ■ Redness or irritation develops

■ If condition persists for more than 3 days

Keep out of reach of children

If swallowed contact a doctor or Poison Control Center immediately.

Directions

■ Rub dime sized amount between hands until dry ■ Supervise children in the use of this product ■ in the case of eye contact, rinse eyes thoroughly with water

Other information

■ Store below 105F ■ May discolor some fabrics

Inactive Ingredients

Water, Glycerin, Propylene Glycol, PEG-40 Hydrogenated Castor Oil, Triethanolamine, Carbomer, Fragrance, Tocopherol, Simmondsia Chinensis (Jooba) Seed Oil, Benzophenone-4,FDC Red 40, DC Red 33